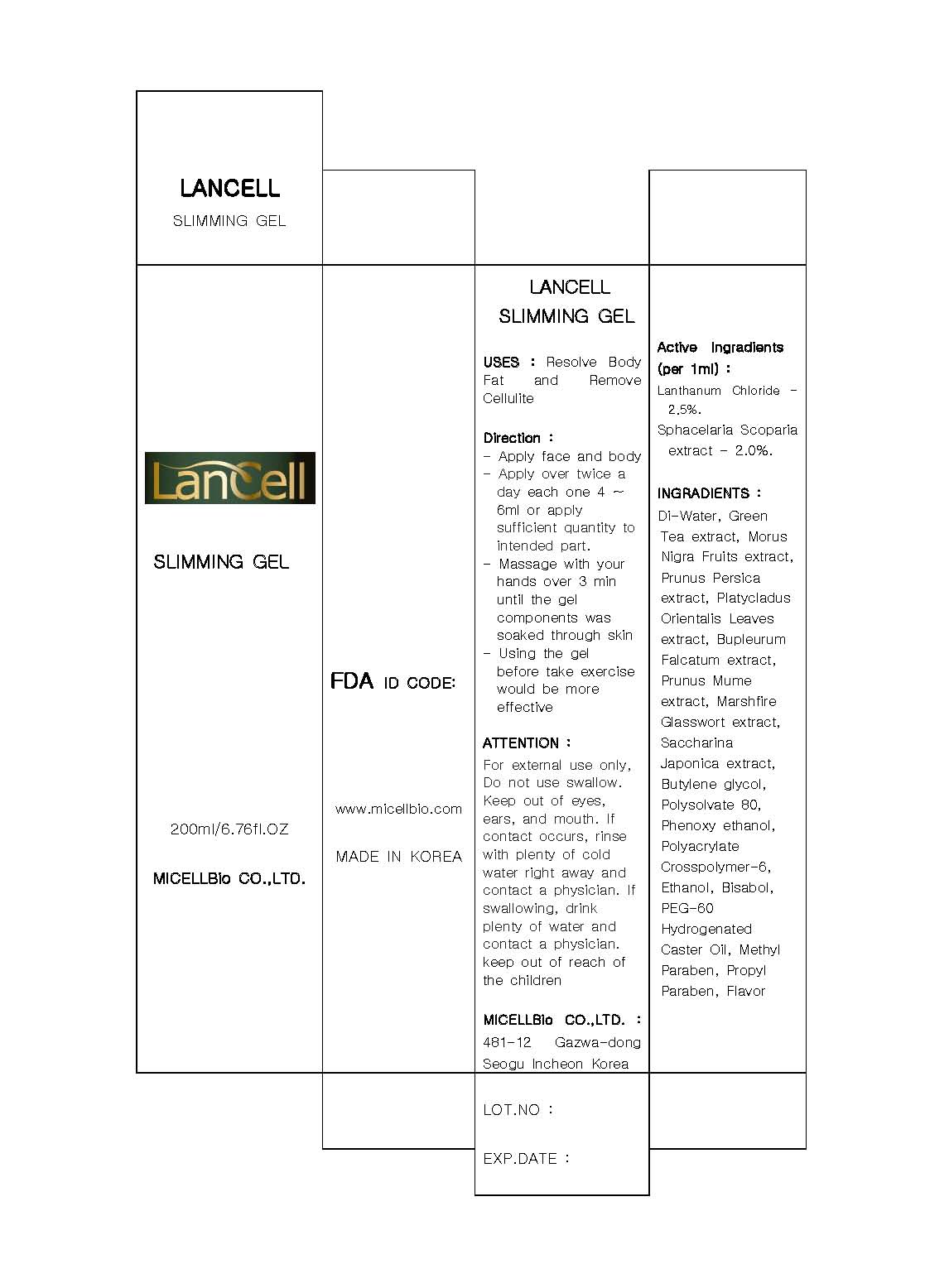 DRUG LABEL: Lancell Slimming
NDC: 76084-3001 | Form: GEL
Manufacturer: MICELLBio Co., Ltd
Category: otc | Type: HUMAN OTC DRUG LABEL
Date: 20110819

ACTIVE INGREDIENTS: LANTHANUM 2.5 mL/100 mL; STYPOCAULON SCOPARIUM 2 mL/100 mL
INACTIVE INGREDIENTS: WATER; GREEN TEA LEAF; POLYSORBATE 80; MORUS NIGRA FRUIT; PEACH; PLATYCLADUS ORIENTALIS LEAF; BUPLEURUM FALCATUM ROOT; PRUNUS MUME FLOWER; SACCHAROMYCES CEREVISIAE; BUTYLENE GLYCOL; ETHANOLAMINE HYDROCHLORIDE; POLYETHYLENE GLYCOL 3000; METHYLPARABEN; PROPYLPARABEN

Drug Facts

active ingredient: lanthanum chloride, sphacelaria scoparia extract

inactive ingredient: di-water, morus nigra fruits extract, pronus persica extract, platychadus orientalis extract, marchfire glasswort extract, saccharina japonica extract, butylene glycol, polysorbate 80, phenoxy ethanol, polyacrylate crosspolymer-6, ethanol, bisabol, PEG-60, hydrogenated caster oil, methyl paraben, propyl paraben, flavor

PURPOSE

resolve body fat

keep out of reach of the children

INDICATIONS AND USAGE

- apply face and body
- apply over twice a day each one 4~6 ml or apply sufficient quantity to intended part
- massage with your hands over 3 minutes until the gel components was soaked through skin
- using the gel before taking exercise would be more effective

WARNINGS

- for external use only
- do not swallow
- keep out of eyes, ears and mouth

DOSAGE AND ADMINISTRATION

- remove cellulite from the body